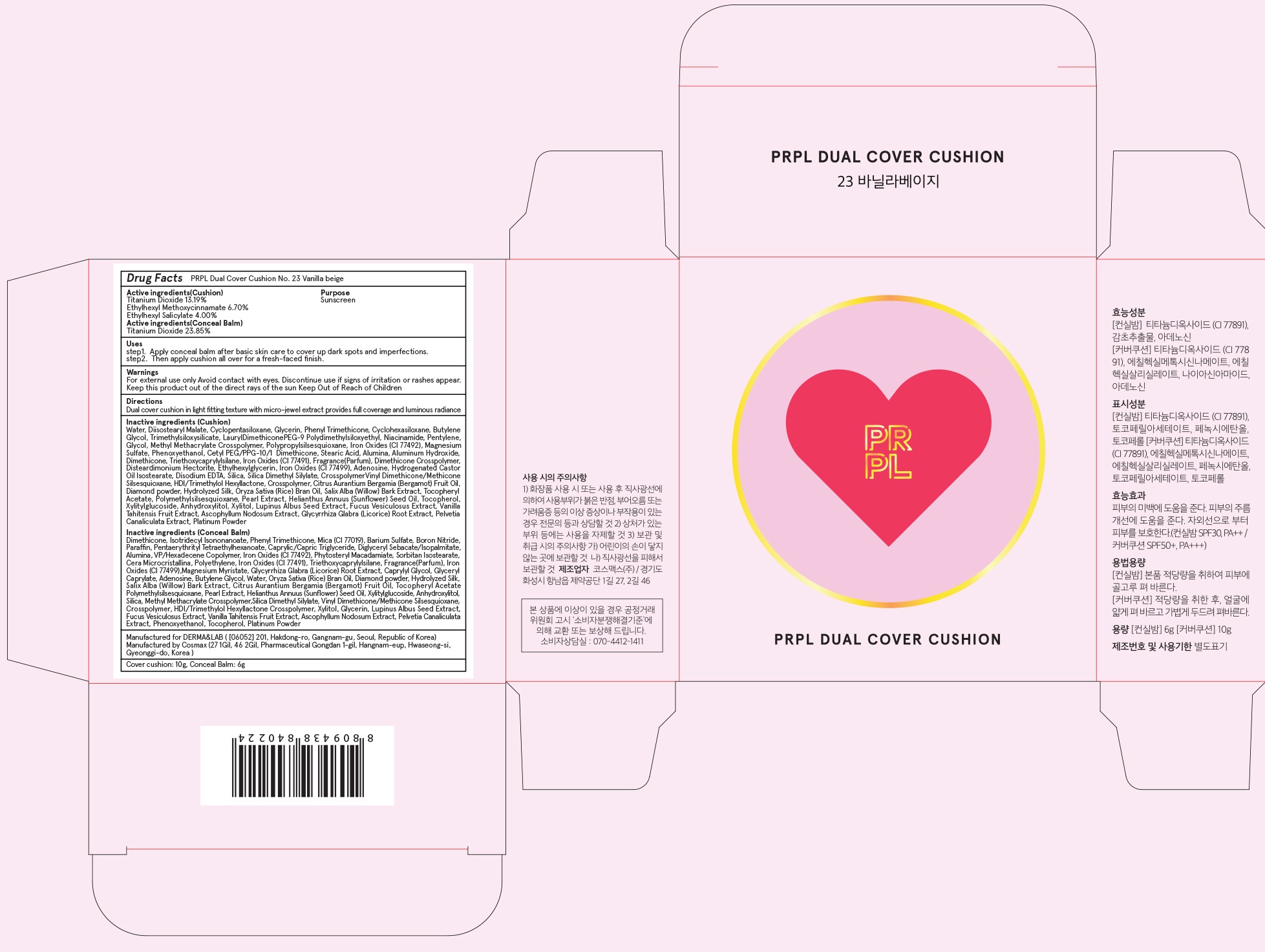 DRUG LABEL: PRPL dual cover cushion No 23 vanilla beige Cushion
NDC: 71725-030 | Form: POWDER
Manufacturer: Derma&lab Co., Ltd.
Category: otc | Type: HUMAN OTC DRUG LABEL
Date: 20171018

ACTIVE INGREDIENTS: Titanium Dioxide 1.31 g/10 g; Octinoxate 0.67 g/10 g; Octisalate 0.40 g/10 g
INACTIVE INGREDIENTS: Water; Diisostearyl Malate

ACTIVE INGREDIENT

Active ingredients: Titanium Dioxide 13.19%, Ethylhexyl Methoxycinnamate 6.70%, Ethylhexyl Salicylate 4.00%

INACTIVE INGREDIENT

Inactive ingredients: Water, Diisostearyl Malate, Cyclopentasiloxane, Glycerin, Phenyl Trimethicone , Cyclohexasiloxane, Butylene Glycol, Trimethylsiloxysilicate, LaurylDimethiconePEG-9 Polydimethylsiloxyethyl, Niacinamide, Pentylene, Glycol, Methyl Methacrylate Crosspolymer, Polypropylsilsesquioxane, Iron Oxides (CI 77492), Magnesium Sulfate, Phenoxyethanol, Cetyl PEG/PPG-10/1 Dimethicone, Stearic Acid, Alumina, Aluminum Hydroxide, Dimethicone, Triethoxycaprylylsilane, Iron Oxides (CI 77491), Fragrance(Parfum), Dimethicone Crosspolymer, Disteardimonium Hectorite, Ethylhexylglycerin, Iron Oxides (CI 77499), Adenosine, Hydrogenated Castor Oil Isostearate, Disodium EDTA, Silica, Silica Dimethyl Silylate, CrosspolymerVinyl Dimethicone/Methicone Silsesquioxane, HDI/Trimethylol Hexyllactone, Crosspolymer, Citrus Aurantium Bergamia (Bergamot) Fruit Oil, Diamond powder, Hydrolyzed Silk, Oryza Sativa (Rice) Bran Oil, Salix Alba (Willow) Bark Extract, Tocopheryl Acetate, Polymethylsilsesquioxane, Pearl Extract, Helianthus Annuus (Sunflower) Seed Oil, Tocopherol, Xylitylglucoside, Anhydroxylitol, Xylitol, Lupinus Albus Seed Extract, Fucus Vesiculosus Extract, Vanilla Tahitensis Fruit Extract, Ascophyllum Nodosum Extract, Glycyrrhiza Glabra (Licorice) Root Extract, Pelvetia Canaliculata Extract, Platinum Powder

PURPOSE

Purpose: Sunscreen

WARNINGS

Warnings: For external use only. Avoid contact with eyes. Discontinue use if signs of irritation or rashes appear. Keep this product out of the direct rays of the sun. Keep Out of Reach of Children.

DESCRIPTION

Uses:

step1. Apply conceal balm after basic skin care to cover up dark spots and imperfections.

step2. Then apply cushion all over for a fresh-faced finish.

Directions: Dual cover cushion in light fitting texture with micro-jewel extract provides full coverage and luminous radiance